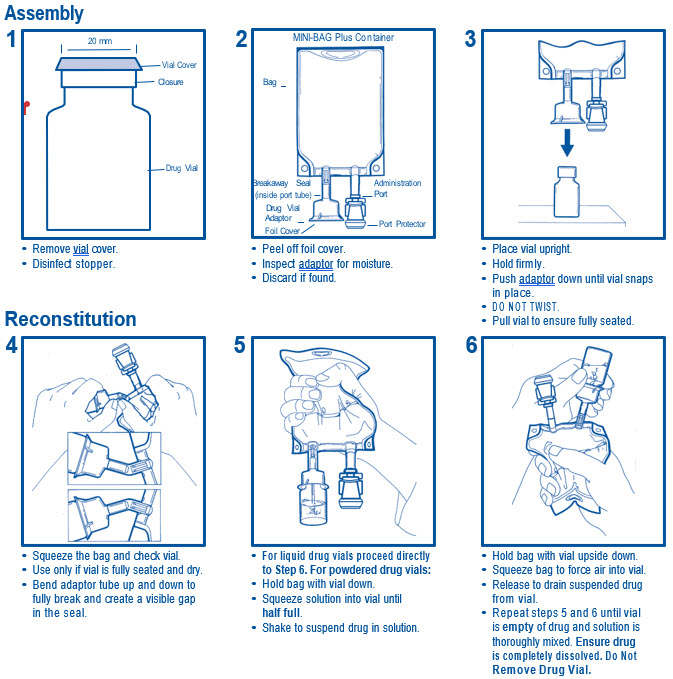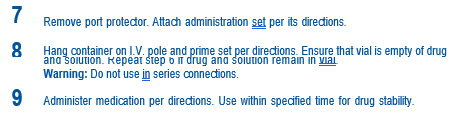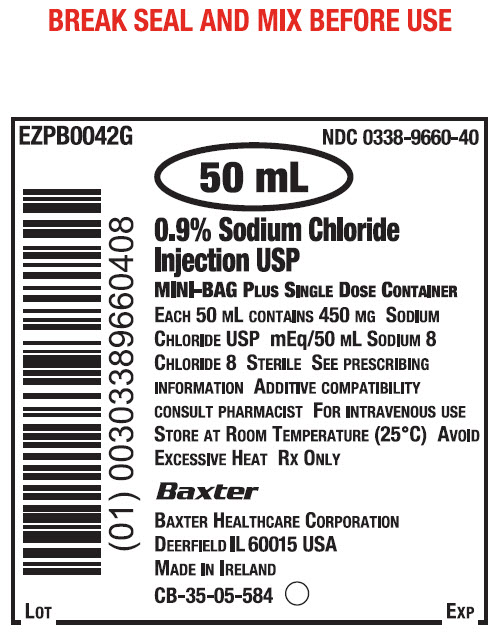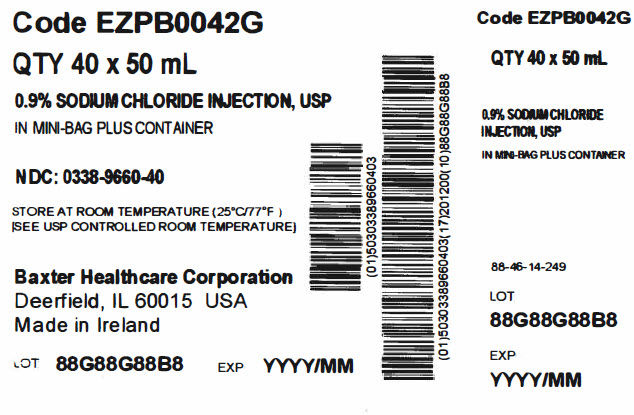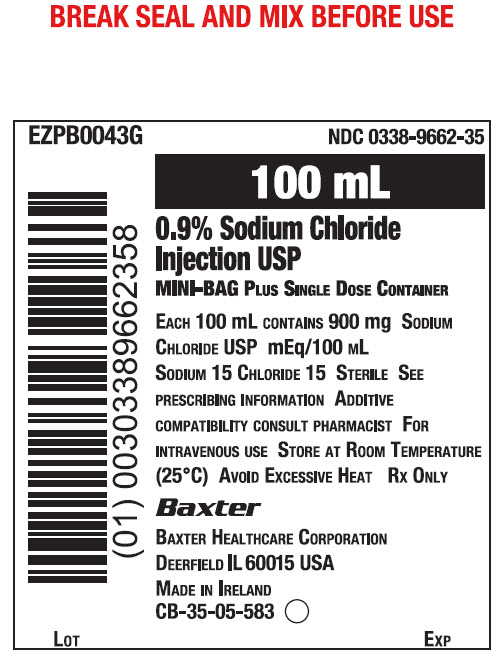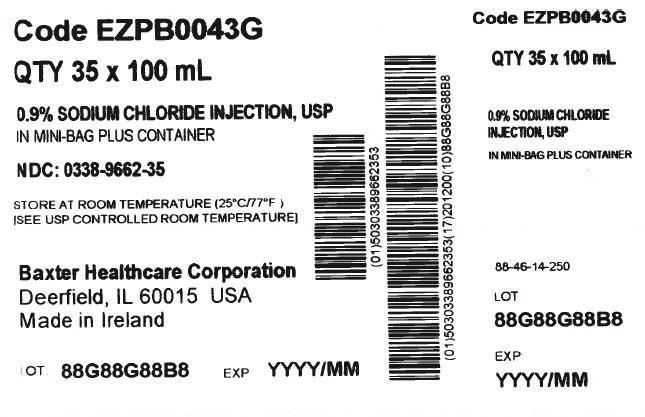 DRUG LABEL: SODIUM CHLORIDE
NDC: 0338-9660 | Form: INJECTION
Manufacturer: Baxter Healthcare Corporation
Category: prescription | Type: HUMAN PRESCRIPTION DRUG LABEL
Date: 20250730

ACTIVE INGREDIENTS: SODIUM CHLORIDE 450 mg/50 mL
INACTIVE INGREDIENTS: WATER

0.9% Sodium Chloride Injection, USP
in Mini-Bag Plus Container

DESCRIPTION

0.9% Sodium Chloride Injection, USP in the MINI-BAG Plus Container is a sterile, nonpyrogenic solution for intravenous administration after admixture with a single dose powdered or liquid (up to 10 mL) drug vial. It contains no antimicrobial agents. The nominal pH is 5.0 (4.5 to 7.0). Each 100 mL contains 900 mg of Sodium Chloride, USP (NaCl). The osmolarity is 308 mOsmol/L (calculated). Hydrochloric Acid, NF or Sodium Hydroxide, NF may be added for pH adjustment. It contains 154 mEq/L sodium and 154 mEq/L chloride.

The MINI-BAG Plus Container is a standard diluent container with an integral drug vial adaptor. It allows for drug admixture after connection to a single dose powdered or liquid (up to 10 mL) drug vial having a 20 mm closure. A breakaway seal in the tube between the vial adaptor and the container is broken to allow transfer of the diluent into the vial and reconstitution of the drug. The MiniBag Plus product mechanically prohibits the transfer of contaminants into and out of the system during and after docking, minimizing environmental and personal exposure. The reconstituted drug is then transferred from the vial into the container diluent and mixed to result in an admixture for delivery to the patient.

The VIAFLEX Plastic Container is fabricated from a specially formulated polyvinyl chloride (PL 146 Plastic). Exposure to temperatures above 25°C/77°F during transport and storage will lead to minor losses in moisture content. Higher temperatures lead to greater losses. It is unlikely that these minor losses will lead to clinically significant changes within the expiration period. The amount of water that can permeate from inside the container into the overwrap is insufficient to affect the solution significantly. Solutions in contact with the plastic container can leach out certain chemical components from the plastic in very small amounts. However, biological testing was supportive of the safety of the plastic container materials.

CLINICAL PHARMACOLOGY

Sodium Chloride Injection, USP has value as a source of water and electrolytes. It is capable of inducing diuresis depending on the clinical condition of the patient.

INDICATIONS AND USAGE

0.9% Sodium Chloride Injection, USP is indicated as a source of water and electrolytes and may also be used as diluent for reconstitution of a powdered or liquid (up to 10 mL) drug product packaged in a vial with a 20 mm closure.

CONTRAINDICATIONS

None known.

WARNINGS

Hypersensitivity

Hypersensitivity and infusion reactions, including hypotension, pyrexia, tremor, chills, urticaria, rash, and pruritus have been reported with 0.9% Sodium Chloride Injection, USP.

Stop the infusion immediately if signs or symptoms of a hypersensitivity reaction develop, such as tachycardia, chest pain, dyspnea and flushing. Appropriate therapeutic countermeasures must be instituted as clinically indicated.

Electrolyte Imbalances

Fluid Overload

Depending on the volume and rate of infusion, and the patient’s underlying clinical condition, the intravenous administration of Sodium Chloride Injection, USP can cause fluid distrurbance such as overhydration/hypervolemia and congested states, including pulmonary congestion and edema.

Avoid 0.9% Sodium Chloride Injection, USP in patients with or at risk for fluid and/or solute overloading. If use cannot be avoided, fluid balance, electrolyte concentrations, and acid base balance, as needed and especially during prolonged use.

Hyponatremia

0.9% Sodium Chloride Injection, USP may cause hyponatremia. Hyponatremia can lead to acute hyponatremic encephalopathy characterized by headache, nausea, seizures, lethargy, and vomiting. Patients with brain edema are at particular risk of severe, irreversible and life-threatening brain injury.

The risk of hospital-acquired hyponatremia is increased in patients with cardiac or pulmonary failure, and in patients with non-osmotic vasopressin release (including SIADH) treated with high volume of Sodium Chloride Injection, USP.

The risk for hyponatremia is increased in pediatric patients, elderly patients, postoperative patients, in those with psychogenic polydipsia, and in patients treated with medications that increase the risk of hyponatremia (such as diuretics, certain antiepileptic and psychotropic medications). See DRUG INTERACTIONS.

Patients at increased risk for developing complications of hyponatremia such as hyponatremic encephalopathy, include pediatric patients, women (in particular pre-menopausal women), patients with hypoxemia, and patients with underlying central nervous system disease. Avoid 0.9% Sodium Chloride Injection, USP in patients with or at risk for hyponatremia. If use cannot be avoided, monitor serum sodium concentrations.

Rapid correction of hyponatremia is potentially dangerous with risk of serious neurologic complications. Brain adaptations reducing risk of cerebral edema make the brain vulnerable to injury when chronic hyponatremia is too rapidly corrected, which is known as osmotic demyelination syndrome (ODS). To avoid complications, monitor serum sodium and chloride concentrations, fluid status, acid-base balance, and signs of neurologic complications.

Hypernatremia

Hypernatremia may occur with Sodium Chloride Injection, USP. Conditions that may increase the risk of hypernatremia, fluid overload and edema (central and peripheral), include patients with: primary hyperaldosteronism; secondary hyperaldosteronism associated with, for example, hypertension, congestive heart failure, liver disease (including cirrhosis). renal disease (including renal artery stenosis, nephrosclerosis); and pre-eclampsia.

Certain medications, such as corticosteroids or corticotropin, may also increase risk of sodium and fluid retention, see DRUG INTERACTIONS.

Avoid 0.9% Sodium Chloride Injection, USP in patients with, or at risk for, hypernatremia. If use cannot be avoided, monitor serum sodium concentrations.

Rapid correction of hypernatremia is potentially dangerous with risk of serious neurologic complications. Excessively rapid correction of hypernatremia is also associated with a risk for serious neurologic complications such as osmotic demyelination syndrome (ODS) with risk of seizures and cerebral edema.

For use only with a single dose powdered or liquid (up to 10 mL) drug vial with a 20 mm closure.

Do not administer unless drug is completely dissolved and drug vial is empty. Do not remove drug vial at any time prior to or during administration.

PRECAUTIONS

Patients with Severe Renal Impairment

Administration of 0.9%Sodium Chloride Injection, USP in patients with or at risk of severe renal impairment, may result in hypernatremia and/or fluid overload (see WARNINGS). Avoid Sodium Chloride Injection, USP in patients with severe renal impairment or conditions that may cause sodium and/or potassium retention, fluid overload, or edema. If use cannot be avoided, monitor patients with severe renal impairment for development of these adverse reactions.

Drug Interactions

Other Products that Affect Fluid and/or Electrolyte Balance

Administration of Sodium Chloride Injection, USP to patients treated concomitantly with drugs associated with sodium and fluid retention, may increase the risk of hypernatremia and volume overload. Avoid use of Sodium Chloride Injection, USP in patients receiving such products, such as corticosteroids or corticotropin. If use cannot be avoided, monitor serum electrolytes, fluid balance and acid-base balance.

Lithium

Renal sodium and lithium clearance may be decreased during administration of Sodium Chloride Injection, USP. Monitor serum may result in increased lithium concentrations during concomitant use.

Renal sodium and lithium clearance may be increased during administration of Sodium Chloride Injection, USP. Monitor serum lithium concentrations during concomitant use.

Other Drugs that Increase the Risk of Hyponatremia

Administration of 0.9% Sodium Chloride Injection, USP in patients treated concomitantly with medications associated with hyponatremia may increase the risk of developing hyponatremia.

Avoid use of 0.9% Sodium Chloride Injection, USP in patients receiving products, such as diuretics, and certain antiepileptic and psychotropic medications. Drugs that increase the vasopressin effect reduce renal electrolyte free water excretion and may also increase the risk of hyponatremia following treatment with intravenous fluids. If use cannot be avoided, monitor serum sodium concentrations.

Pregnancy

There are no adequate and well controlled studies with Sodium Chloride Injection, USP, in pregnant women and animal reproduction studies have not been conducted with this drug. Therefore, it is not known whether Sodium Chloride Injection, USP can cause fetal harm when administered to a pregnant woman. Sodium Chloride Injection, USP should be given during pregnancy only if the potential benefit justifies the potential risk to the fetus.

Nursing Mothers

It is not known whether this drug is present in human milk. Because many drugs are present in human milk, caution should be exercised when Sodium Chloride Injection, USP is administered to a nursing woman.

Pediatric Use

The use of Sodium Chloride Injection, USP in pediatric patients is based on clinical practice. (See DOSAGE AND ADMINISTRATION.)

Closely monitor plasma electrolyte concentrations in pediatric patients who may have impaired ability to regulate fluids and electrolytes. In very low birth weight infants, excessive or rapid administration of Sodium Chloride Injection, USP may result in increased serum osmolality and risk of intracerebral hemorrhage.

Children (including neonates and older children) are at increased risk of developing hyponatremia as well as for developing hyponatremic encephalopathy.

Geriatric Use

Geriatric patients are at increased risk of developing electrolyte imbalances. Sodium Chloride Injection, USP is known to be substantially excreted by the kidney, and the risk of toxic reactions to this drug may be greater in patients with impaired renal function.

Therefore, dose selection for an elderly patient should be cautious, usually starting at the low end of the dosing range, reflecting the greater frequency of decreased hepatic, renal, or cardiac function, and of concomitant disease or other drug therapy. Consider monitoring renal function in elderly patients.

ADVERSE REACTIONS

Post-Marketing Adverse Reactions

The following adverse reactions have been identified during postapproval use of 0.9% Sodium Chloride Injection, USP. Because these reactions are reported voluntarily from a population of uncertain size, it is not always possible to reliably estimate their frequency or establish a causal relationship to drug exposure.

The following adverse reactions have been reported in the post-marketing experience during use of 0.9% Sodium Chloride Injection, USP and include the following:

Hypersensitivity reactions: hypersensitivity/infusion reactions, including hypotension, pyrexia, tremor, chills, urticaria, rash, and pruritus.

General disorders and administration site conditions: infusion site reactions, such as infusion site erythema, injection site streaking, burning sensation, and infusion site urticaria.

Metabolism and nutrition disorders: hypernatremia, hyperchloremic metabolic acidosis, and hyponatremia, which may be symptomatic.

Nervous System Disorders: Hyponatremic encephalopathy.

If an adverse reaction does occur, discontinue the infusion, evaluate the patient, institute appropriate therapeutic countermeasures and save the remainder of the fluid for examination if deemed necessary.

OVERDOSAGE

Excessive administration of:

- 0.9% Sodium Chloride Injection, USP can cause hypernatremia.
- 0.9% Sodium Chloride Injection, USP can cause fluid overload (which can lead to pulmonary and/or peripheral edema). See WARNINGS and ADVERSE REACTIONS.

When assessing an overdose, any additives in the solution must also be considered. The effects of an overdose may require immediate medical attention and treatment.

Interventions include discontinuation of Sodium Chloride Injection, USP administration, dose reduction, and other measures as indicated for the specific clinical constellation (e.g., monitoring of fluid balance, electrolyte concentrations and acid base balance).

DOSAGE AND ADMINISTRATION

Important Administration Instructions

- 0.9 % Sodium Chloride Injection, USP is intended for intravenous administration using sterile equipment.
- Do not connect flexible plastic containers in series in order to avoid air embolism due to possible residual air contained in the primary container.
- Set the vent to the closed position on a vented intravenous administration set to prevent air embolism.
- Use a dedicated line without any connections to avoid air embolism.
- Do not pressurize intravenous solutions contained in flexible plastic containers to increase flow rates.
- Prior to infusion, visually inspect the solution for particulate matter and discoloration. The solution should be clear and there should be no precipitates. Do not administer unless solution is clear, and container is undamaged.

Dosing Information

The choice of product, dosage, volume, rate, and duration of administration is dependent upon the age, weight and clinical condition of the patient and concomitant therapy, and administration should be determined by a physician experienced in intravenous fluid therapy.

Introduction of Additives

Additives may be incompatible.

Evaluate all additions to the plastic container for compatibility and stability of the resulting preparation. Consult with a pharmacist, if available.

If, in the informed judgement of the physician, it is deemed advisable to introduce additives, use aseptic technique. Mix thoroughly when additives have been introduced. After addition, if there is a discoloration and/or the appearance of precipitates, insoluble complexes or crystals, do not use. Do not store solutions containing additives. Discard any unused portion.

HOW SUPPLIED

0.9% Sodium Chloride Injection, USP in MINI-BAG Plus Container is available as follows:

Code | Size (mL) | NDC
EZPB0042G | 50 | 0338-9660-40
EZPB0043G | 100 | 0338-9662-35

Exposure of pharmaceutical products to heat should be minimized. Avoid excessive heat. It is recommended the product be stored at room temperature (25°C/77°F).

DIRECTIONS FOR USE

For Information on Risk of Air Embolism – see DOSAGE AND ADMINISTRATION.

To Open

Tear overwrap down side at slit and remove solution container. Visually inspect the container. If the outlet port protector is damaged, detached, or not present, discard container as solution path sterility may be impaired. Some opacity of the plastic due to moisture absorption during the sterilization process may be observed. This is normal and does not affect the solution quality or safety. The opacity will diminish gradually.

Prior to use, check that the vial adaptor cover is intact. Check the solution container for minute leaks by squeezing inner bag firmly. If leaks are found or if the vial adaptor cover is not intact, discard product as sterility may be impaired.

To Assemble and Reconstitute

See diagram for detailed instructions.

MINI-BAG Plus Container Directions
Only For Single Dose Powdered or Liquid (up to 10 mL) Drug Vials with 20 mm Closures
Use Aseptic Technique

Baxter Healthcare Corporation
Deerfield, IL 60015 USA
Printed in Ireland

Baxter, Mini-Bag Plus and Viaflex are trademarks of Baxter International Inc.

CB-30-03-107
Rev. November 2024

PACKAGE/LABEL PRINCIPAL DISPLAY PANEL

Container Label

BREAK SEAL AND MIX BEFORE USE

EZPB0042G
NDC 0338-9660-40

BarCode
(01) 00303389660408

50 mL
0.9% Sodium Chloride
Injection USP
MINI-BAG Plus Single Dose Container

EACH 50 ML CONTAINS 450 MG SODIUM
CHLORIDE USP MEQ/50 ML SODIUM 8
CHLORIDE 8 STERILE SEE PRESCRIBING
INFORMATION ADDITIVE COMPATIBILITY
CONSULT PHARMACIST FOR INTRAVENOUS USE
STORE AT ROOM TEMPERATURE (25°C) AVOID
EXCESSIVE HEAT RX ONLY

Baxter Logo
Baxter Healthcare Corporation
Deerfield, IL 60015 USA
Made in Ireland
CB-35-03-584

Lot
Exp

Carton Label

Code EZPB0042G

QTY 40 x 50 mL

0.9% SODIUM CHLORIDE INJECTION, USP
IN MINI-BAG PLUS CONTAINER

NDC: 0338-9660-40

STORE AT ROOM TEMPERATURE (25°C/77°F)
[SEE USP CONTROLLED ROOM TEMPERATURE]

Baxter Healthcare Corporation
Deerfield, IL 60015 USA
Made in Ireland

LOT 88G88G88B8
EXP YYYY/MM

BarCode
(01)50303389660403

BarCode
(01)503389660403(17)201200(10)88G88G88B8

Code EZPB0042G

QTY 40 x 50 mL

0.9% SODIUM CHLORIDE
INJECTION, USP
IN MINI-BAG PLUS CONTAINER

88-46-14-249

LOT
88G88G88B8

EXP
YYYY/MM

Container Label

BREAK SEAL AND MIX BEFORE USE

EZPB0043G
NDC 0338-9662-35

100 Ml
0.9% Sodium Chloride
Injection USP
MINI-BAG PLUS SINGLE DOSE CONTAINER

BarCode
(01) 00303389662358

EACH 100 ML CONTAINS 900 MG SODIUM
CHLORIDE USP MEQ/100 ML
SODIUM 15 CHLORIDE 15 STERILE SEE
PRESCRIBING INFORMATION ADDITIVE
COMPATIBILITY CONSULT PHARMACIST FOR
INTRAVENOUS USE STORE AT ROOM TEMPERATURE
(25°C) AVOID EXCESSIVE HEAT RX ONLY

Baxter Logo
Baxter Healthcare Corporation
Deerfield, IL 60015 USA
Made in Ireland
CB-35-05-583

LOT
EXP

Carton Label

Code EZPB0043G

QTY 35 x 100 mL

0.9% SODIUM CHLORIDE INJECTION, USP
IN MINI-BAG PLUS CONTAINER

NDC: 0338-9662-35

STORE AT ROOM TEMPERATURE (25°C/77°F)
[SEE USP CONTROLLED ROOM TEMPERATURE]

Baxter Healthcare Corporation
Deerfield, IL 60015 USA
Made in Ireland

LOT 88G88G88B8
EXP YYYY/MM

BarCode
(01)50303389662353

BarCode
(01)503389662353(17)201200(10)88G88G88B8

Code EZPB0043G

QTY 35 x 100 mL

0.9% SODIUM CHLORIDE
INJECTION, USP
IN MINI-BAG PLUS CONTAINER

88-46-14-250

LOT
88G88G88B8

EXP
YYYY/MM